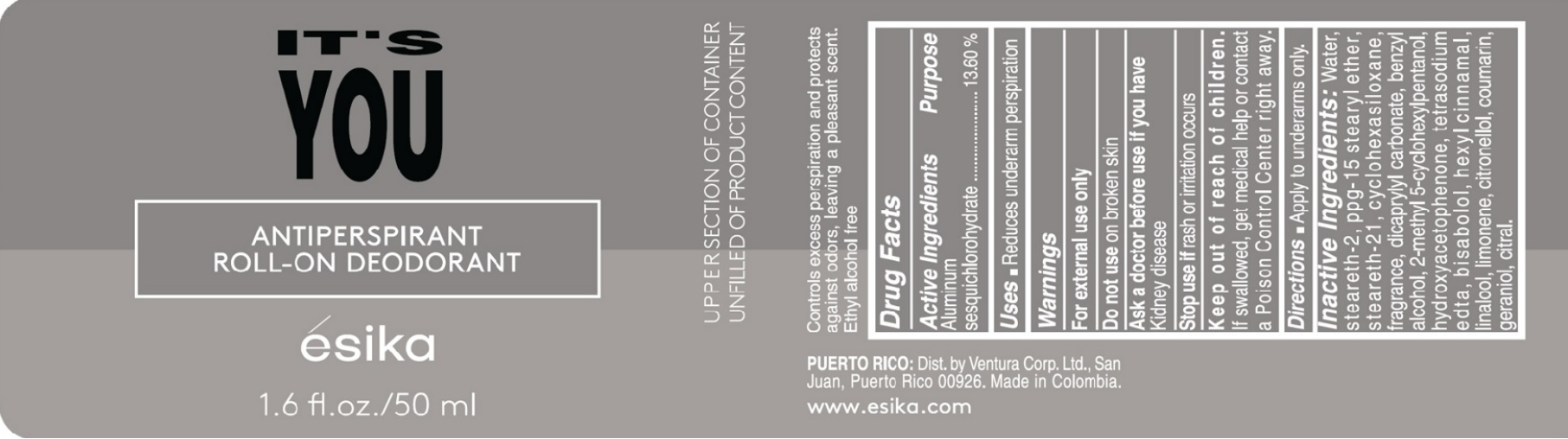 DRUG LABEL: Its you Antiperspirant Roll-on Deodorant
NDC: 14141-213 | Form: EMULSION
Manufacturer: BEL STAR S A
Category: otc | Type: HUMAN OTC DRUG LABEL
Date: 20241028

ACTIVE INGREDIENTS: ALUMINUM SESQUICHLOROHYDRATE 13.6 g/100 mL
INACTIVE INGREDIENTS: HYDROXYACETOPHENONE; EDETATE SODIUM; BENZYL ALCOHOL; LINALOOL, (+)-; COUMARIN; GERANIOL; PPG-15 STEARYL ETHER; .ALPHA.-HEXYLCINNAMALDEHYDE; STEARETH-21; STEARETH-2; CYCLOMETHICONE 6; DICAPRYLYL CARBONATE; WATER; LIMONENE, (+)-; CITRAL; .BETA.-CITRONELLOL, (R)-; LEVOMENOL; 2-METHYL 5-CYCLOHEXYLPENTANOL

It's you Antiperspirant Roll-on Deodorant

Active Ingredient Purpose
Aluminum sesquichlorohydrate 13.60% Antiperspirant

Uses

- Reduces underarm perspiration

Keep out of reach of children. If swallowed, get medical Help or contact a Poison Control Center right away.

Stop use if rash or irritation occurs

Warnings
For external use only
Do not use on broken skin
Ask a doctor before use if you have kidney disease

Directions

- Apply to underarms only.

INACTIVE INGREDIENT

Inactive ingredients: WATER, STEARETH-2, PPG-15 STEARYL ETHER, STEARETH-21, CYCLOHEXASILOXANE, FRAGRANCE, DICAPRYLYL CARBONATE, BENZYL ALCOHOL, 2-METHYL 5-CYCLOHEXYLPENTANOL, HYDROXYACETOPHENONE, TETRASODIUM EDTA, BISABOLOL, HEXYL CINNAMAL, LINALOOL, LIMONENE, CITRONELLOL, COUMARIN, GERANIOL, CITRAL.

PACKAGE LABEL

It's you

Antiperspirant roll-on Deodorant

esika

1.6 fl. oz./ 50 ml